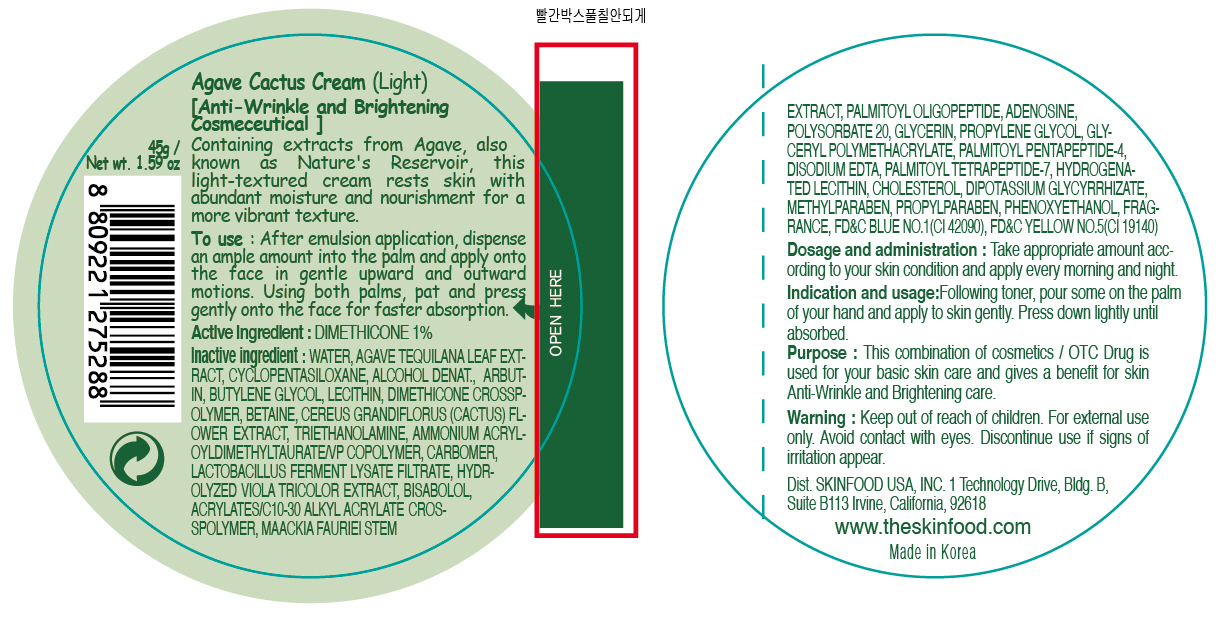 DRUG LABEL: AGAVE CACTUS
NDC: 76214-004 | Form: CREAM
Manufacturer: SKINFOOD CO., LTD.
Category: otc | Type: HUMAN OTC DRUG LABEL
Date: 20110715

ACTIVE INGREDIENTS: DIMETHICONE 0.45 g/45 g
INACTIVE INGREDIENTS: WATER; AGAVE TEQUILANA LEAF; CYCLOMETHICONE 5; ARBUTIN; BUTYLENE GLYCOL; LECITHIN, SOYBEAN; BETAINE; PHENOXYETHANOL; TROLAMINE; METHYLPARABEN; MAACKIA FLORIBUNDA STEM; PALMITOYL OLIGOPEPTIDE; ADENOSINE; PROPYLENE GLYCOL; POLYSORBATE 20; GLYCERIN; EDETATE DISODIUM; PALMITOYL PENTAPEPTIDE-4; PALMITOYL TETRAPEPTIDE-7; HYDROGENATED SOYBEAN LECITHIN; CHOLESTEROL; PROPYLPARABEN

Drug Facts

Active ingredient: DIMETHICONE

Inactive ingredients:

WATER, AGAVE TEQUILANA LEAF EXTRACT, CYCLOPENTASILOXANE, ALCOHOL DENAT., ARBUTIN, BUTYLENE GLYCOL, LECITHIN, DIMETHICONE CROSSPOLYMER, BETAINE, CEREUS GRANDIFLORUS (CACTUS) FLOWER EXTRACT, TRIETHANOLAMINE, AMMONIUM ACRYLOYLDIMETHYLTAURATE/VP COPOLYMER, CARBOMER, LACTOBACILLUS FERMENT LYSATE FILTRATE, HYDROLYZED VIOLA TRICOLOR EXTRACT, BISABOLOL, ACRYLATES/C10-30 ALKYL ACRYLATE CROSSPOLYMER, MAACKIA FAURIEI STEM EXTRACT, PALMITOYL OLIGOPEPTIDE, ADENOSINE, POLYSORBATE 20, GLYCERIN, PROPYLENE GLYCOL, GLYCERYL POLYMETHACRYLATE, PALMITOYL PENTAPEPTIDE-4, DISODIUM EDTA, PALMITOYL TETRAPEPTIDE-7, HYDROGENATED LECITHIN, CHOLESTEROL, DIPOTASSIUM GLYCYRRHIZATE, METHYLPARABEN, PROPYLPARABEN, PHENOXYETHANOL, FRAGRANCE

Purpose:

This combination of cosmetics is used for your basic skin care and gives a benefit for Anti-Wrinkle and Brightening care.

Warnings:

For external use only. Avoid contact with eyes. Discontinue use if signs of irritation appear.

Keep out of reach of children:

Keep out of reach of children.

Indication and usage:

Following emulsion, pour some on the palm of your hand and apply to skin gently. Press down lightly until absorbed.

Dosage and administration:

Take appropriate amount according to your skin condition and apply every morning and night.